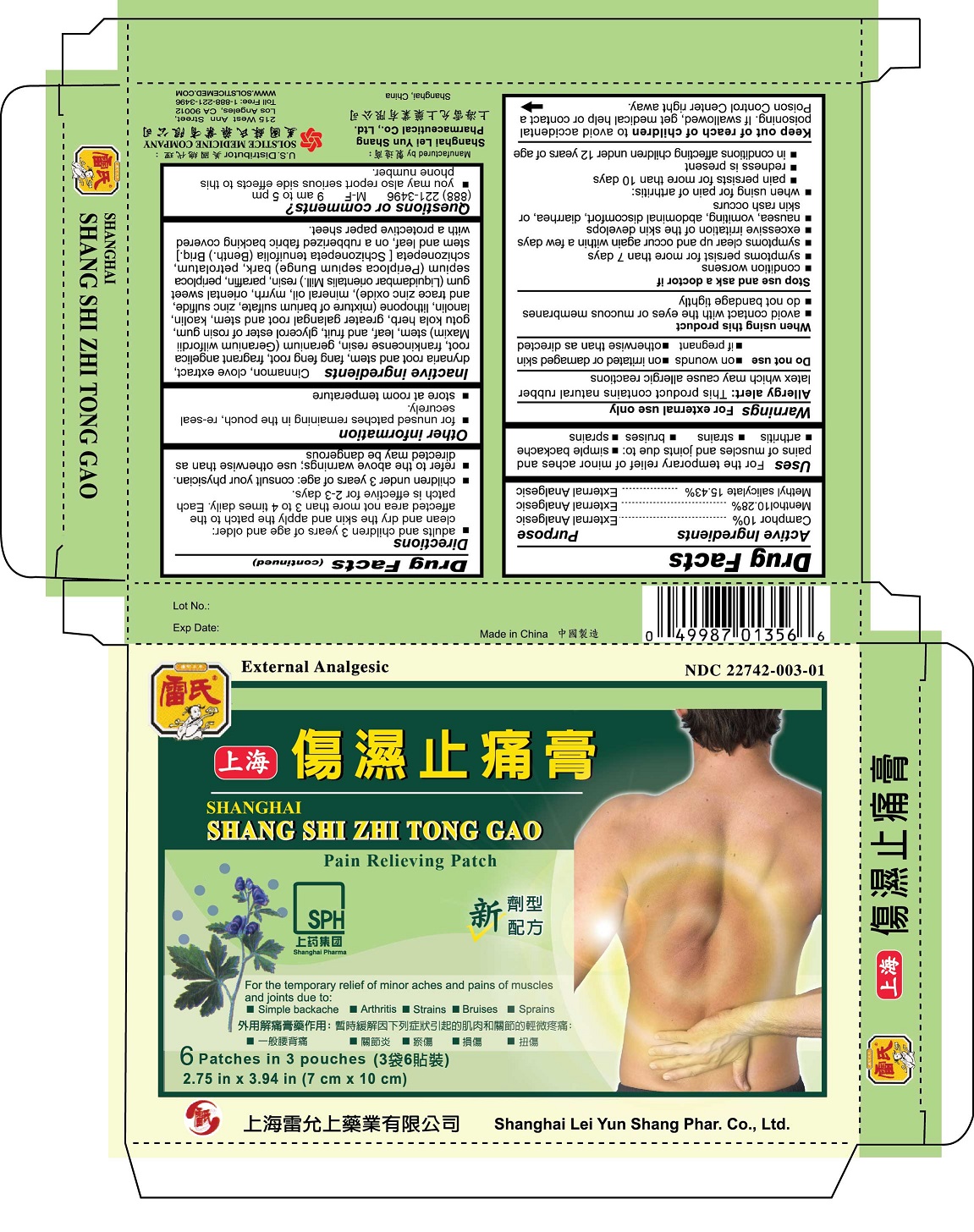 DRUG LABEL: SHANGHAI SHANG SHI ZHI TONG GAO PAIN RELIEVING
NDC: 22742-003 | Form: PATCH
Manufacturer: SHANGHAI LEI YUN SHANG PHARMACEUTICAL CO LTD
Category: otc | Type: HUMAN OTC DRUG LABEL
Date: 20191113

ACTIVE INGREDIENTS: CAMPHOR (SYNTHETIC) 10 1/1 1; MENTHOL 10.28 1/1 1; METHYL SALICYLATE 15.43 1/1 1
INACTIVE INGREDIENTS: CINNAMON; CLOVE; DRYNARIA FORTUNEI ROOT; SAPOSHNIKOVIA DIVARICATA ROOT; ANGELICA DAHURICA ROOT; FRANKINCENSE; GERANIUM WILFORDII WHOLE; ROSIN PARTIALLY DIMERIZED GLYCEROL ESTER; CENTELLA ASIATICA; ALPINIA GALANGA WHOLE; KAOLIN; LANOLIN; BARIUM SULFATE; ZINC SULFIDE; ZINC OXIDE; MINERAL OIL; MYRRH; LIQUIDAMBAR ORIENTALIS WHOLE; PARAFFIN; PERIPLOCA SEPIUM ROOT BARK; PETROLATUM; SCHIZONEPETA TENUIFOLIA WHOLE

Drug Facts

Active ingredients
Camphor 10%
Menthol 10.28%
Methyl salicylate 15.43%

Purpose
External analgesic

Uses
For the temporary relief of minor aches and pains of muscles and joints due to:
simple backache
arthritis
strains
bruises
sprains

Warnings
For external use only

Allergy alert: This product contains natural rubber latex which may cause allergic reactions

Do not use
on wounds
on irritated or damaged skin
if pregnant
otherwise than as directed

When using this product
avoid contact with the eyes or mucous membranes
do not bandage tightly

Stop use and ask a doctor if
condition worsens
symptoms persist for more than 7 days
symptoms clear up and occur again within a few days
excessive irritation of the skin develops
nausea, vomiting, abdominal discomfort, diarrhea, or skin rash occurs
when using for pain of arthritis:
pain persists for more than 10 days
redness is present
in conditions affecting children under 12 years of age

Keep out of reach of children to avoid accidental poisoning. If swallowed, get medical help or contact a Poison Control Center right away.

Directions
adults and children 3 years of age and older: clean and dry the skin and apply the patch to the affected area not than 3 to 4 times daily. Each patch is effective for 2-3 days.
children under 3 years of age: consult your physician.
refer to the above warnings; use otherwise than as directed may be dangerous.

Other information
for unused patches remaining in the pouch, re-seal securely
store at room temperature

INACTIVE INGREDIENT

Inactive ingredientsCinnamon, clove extract, drynaria root and stem, fang feng root, fragrant angelica root, frankincense resin, geranium (Geranium wilfordii Maxim) stem, leaf, and fruit, glycerol ester of rosin gum, gotu kola herb, greater galangal root and stem, kaolin, lanolin, lithopone (mixture of barium sulfate, zinc sulfide, and trace zinc oxide), mineral oil, myrrh, oriental sweet gum (Liquidambar orientalis Mill.) resin, paraffin, periploca sepium (Periploca sepium Bunge) bark, petrolatum, schizonepeta [Schizonepeta tenuifolia (Benth.) Briq.] stem and leaf, on a rubberized fabric backing covered with a protective paper sheet.

Questions or comments? (888) 221-3496 M-F 9 am to 5 pm
you may also report serious side effects to thi phone number

PACKAGE LABEL

SHANGHAI SHANG SHI ZHI TONG GAO

Pain Relieving Patch

External Analgesic

NDC 22742-003-01

6 Patches in 3 Pouches Each Patch 2.75 in x 3.94 in (7 cm x 10 cm)